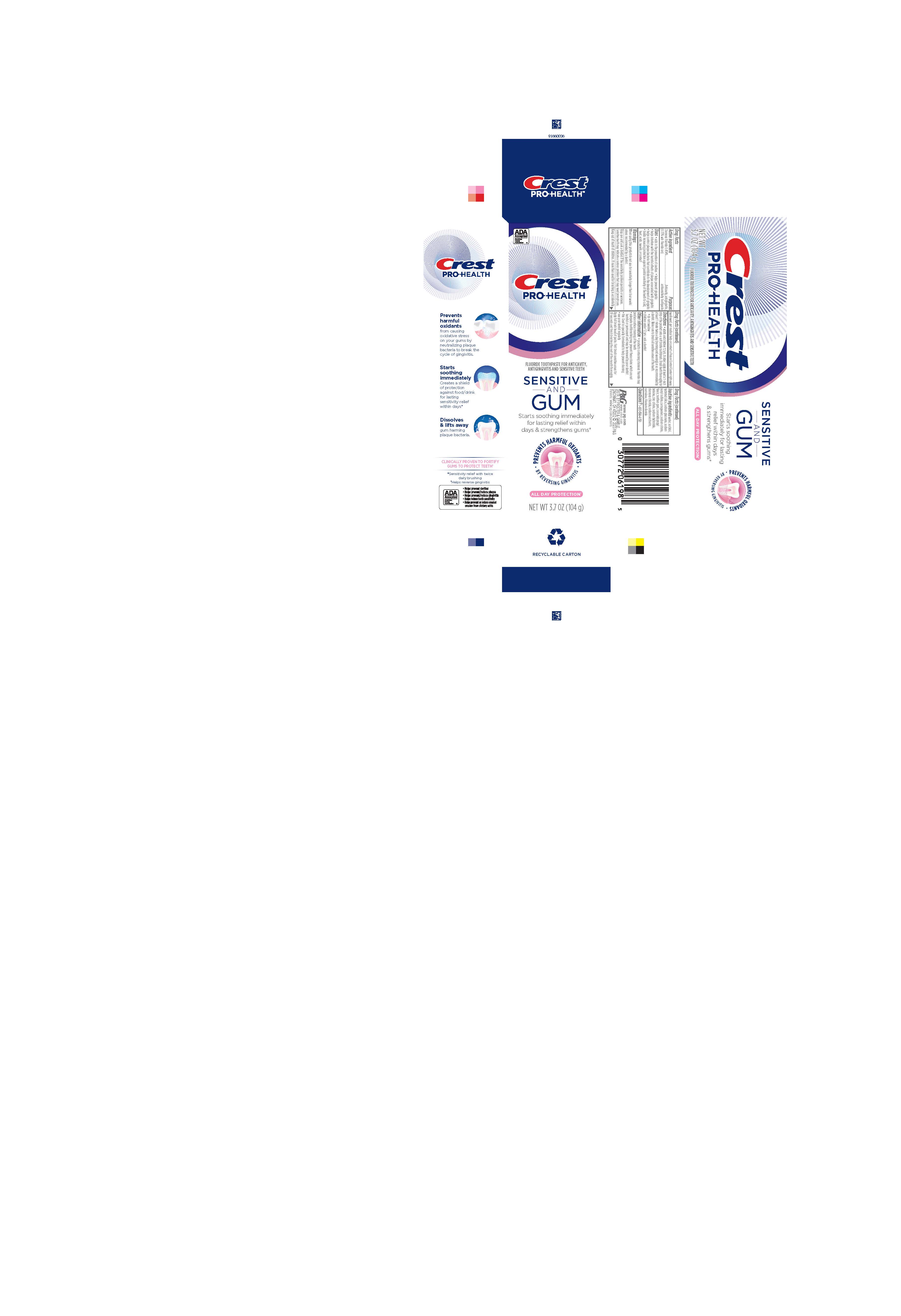 DRUG LABEL: Crest Pro-Health
NDC: 69423-765 | Form: PASTE, DENTIFRICE
Manufacturer: The Procter & Gamble Manufacturing Company
Category: otc | Type: HUMAN OTC DRUG LABEL
Date: 20260108

ACTIVE INGREDIENTS: STANNOUS FLUORIDE 1.5 mg/1 g
INACTIVE INGREDIENTS: SUCRALOSE; HYDRATED SILICA; SORBITOL; SODIUM CITRATE; COCAMIDOPROPYL BETAINE; WATER; SODIUM LAURYL SULFATE; SODIUM GLUCONATE; CARRAGEENAN; SACCHARIN SODIUM; XANTHAN GUM; ZINC CITRATE; SODIUM HYDROXIDE; STANNOUS CHLORIDE; TITANIUM DIOXIDE

Crest Pro-Health Sensitive and Gum All Day Protection

Drug Facts

Active ingredient

Stannous fluoride 0.454% (0.15% w/v fluoride ion)

Purposes

Anticavity, antigingivitis, antisensitivity toothpaste

Uses

- aids in the prevention of cavities
- helps prevent gingivitis
- helps interfere with the harmful effects of plaque associated with gingivitis
- helps control plaque bacteria that contribute to the development of gingivitis
- builds increasing protection against painful sensitivity of the teeth to cold, heat, acids, sweets or contact

Warnings

When using this product do not use for sensitivity longer than four weeks unless recommended by a dentist.

Stop use and ask a dentist if the sensitivity problem persists or worsens. Sensitive teeth may indicate a serious problem that may need prompt care.

Keep out of reach of children. If more than used for brushing is accidentally swallowed, get medical help or contact a Poison Control Center right away.

Directions

- adults and children 12 yrs. & older: apply at least a 1-inch strip of the product onto a soft bristle toothbrush. Brush teeth thoroughly for at least 1 minute twice a day (morning and evening) or as recommended by a dentist. Make sure to brush all sensitive areas of the teeth.
- do not swallow
- children under 12 yrs.: ask a dentist

Other information

- products containing stannous fluoride may produce surface staining of the teeth
- adequate toothbrushing may prevent these stains which are not harmful or permanent and may be removed by your dentist
- this Crest is specially formulated to help prevent staining
- see your dentist regularly

Apply full brush head of paste. First brush sensitive areas for 30 seconds and finish brushing the rest of the mouth thoroughly.

Inactive ingredients

water, sorbitol, hydrated silica, sodium lauryl sulfate, sodium gluconate, carrageenan, sodium citrate, flavor, xanthan gum, cocamidopropyl betaine, zinc citrate, sodium hydroxide, stannous chloride, sodium saccharin, sucralose, titanium dioxide

Questions?

1-800-594-4158

DISTR. BY PROCTER & GAMBLE,
CINCINNATI, OH 45202

PRINCIPAL DISPLAY PANEL - 104 g Tube Carton

ADA Accepted

American Dental Association

Crest

PRO-HEALTH

FLUORIDE TOOTHPASTE FOR ANTICAVITY, ANTIGINGIVITIS AND SENSITIVE TEETH

SENSITIVE AND GUM

Starts soothing immediately for lasting relief within days & strengthens gums*

PREVENTS HARMFUL OXIDANTS

BY REVERSING GINGIVITIS

ALL DAY PROTECTION*

NET WT 3.7 OZ (104 g)